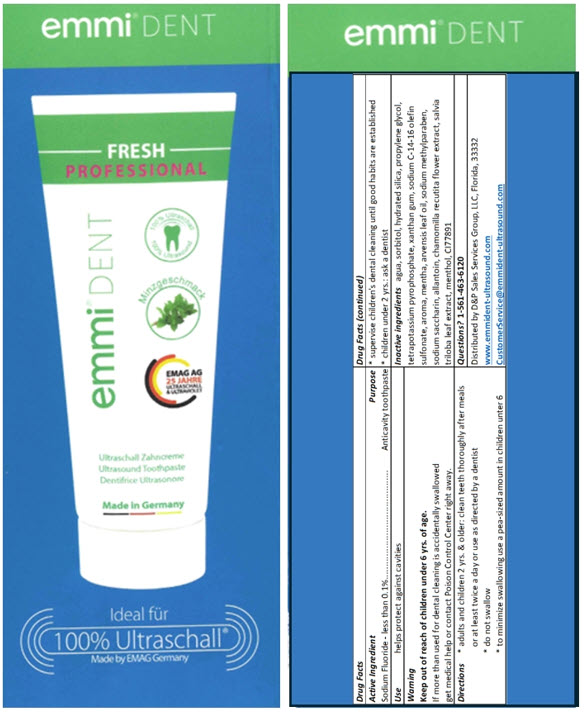 DRUG LABEL: Emmi-dent Fresh
NDC: 63956-004 | Form: PASTE, DENTIFRICE
Manufacturer: EMAG  AG
Category: otc | Type: HUMAN OTC DRUG LABEL
Date: 20241203

ACTIVE INGREDIENTS: Sodium Fluoride 199 mg/75 mL
INACTIVE INGREDIENTS: Water; Sorbitol; Hydrated Silica; Propylene Glycol; POTASSIUM PYROPHOSPHATE; Xanthan Gum; Sodium C14-16 Olefin Sulfonate; Mentha Arvensis Leaf oil; Titanium Dioxide; METHYLPARABEN SODIUM; SACCHARIN SODIUM; Allantoin; CHAMOMILE; THREE-LOBE SAGE; MENTHOL, UNSPECIFIED FORM

Emmi®-dent Fresh

Drug Facts

Active Ingredient

Sodium Fluoride 0.199% (0.11% w/v fluoride ion)

Purpose

Anticavity toothpaste

Use

helps protect against cavities

Warning

Keep out of reach of children under 6 yrs. of age.

If more than used for dental cleaning is accidentally swallowed, get medical help or contact a Poison Control Center right away.

Directions

- adults and children 2 yrs. & older: clean teeth thoroughly after meals or at least twice a day or use as directed by a dentist
- do not swallow
- to minimize swallowing use a pea-sized amount in children unter 6
- supervise children's dental cleaning until good habits are established
- children under 2 yrs.: ask a dentist

Inactive ingredients

water, sorbitol, hydrated silica, propylene glycol, tetrapotassium pyrophosphate, xanthan gum, sodium C-14-16 olefin sulfonate, aroma, mentha arvenis leaf oil, titanium dioxide, sodium methyl paraben, sodium saccharin, allantoin, chamomilla recutita (matricaria) flower extract, salvia triloba leaf extract

Questions?

1-833-682-8902

Distributed by Ultra Oral Care Inc. , Spring, Texas, 77386

www.emmident-ultrasound.com

PRINCIPAL DISPLAY PANEL - 75 ml Tube Carton

emmi® DENT

FRESH
PROFESSIONAL

emmi® DENT

100% ULTRASOUND

Ultrasound Toothpaste

Made in Germany

Ideal

100% Ultraschall®

Made by EMAG Germany